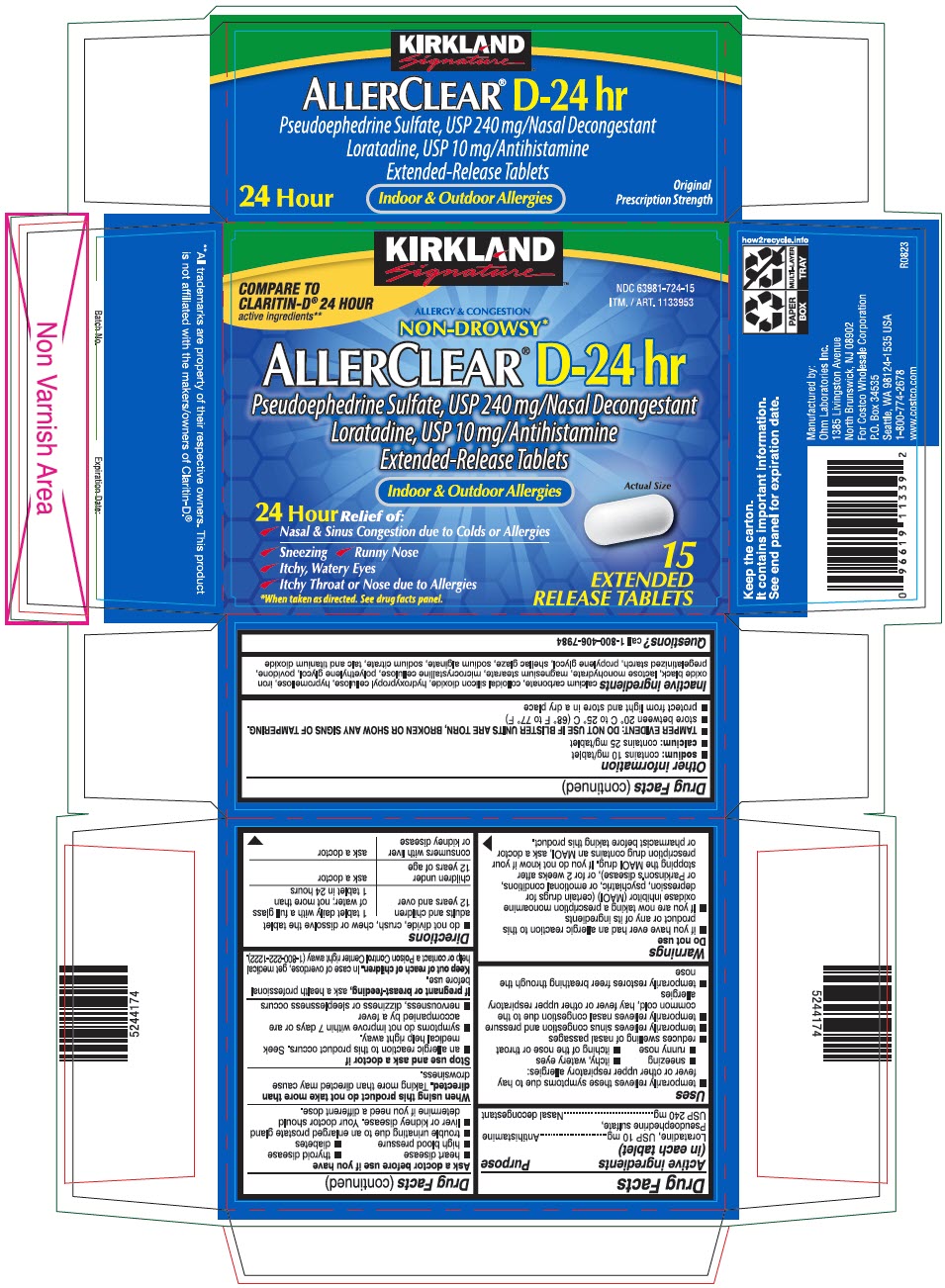 DRUG LABEL: KIRKLAND SIGNATURE ALLERCLEAR D 24 HR
NDC: 63981-724 | Form: TABLET, EXTENDED RELEASE
Manufacturer: Kirkland-COSTCO WHOLESALE COMPANY
Category: otc | Type: HUMAN OTC DRUG LABEL
Date: 20230823

ACTIVE INGREDIENTS: loratadine 10 mg/1 1; pseudoephedrine sulfate 240 mg/1 1
INACTIVE INGREDIENTS: calcium carbonate; silicon dioxide; hydroxypropyl cellulose, unspecified; hypromellose, unspecified; ferrosoferric oxide; lactose monohydrate; magnesium stearate; microcrystalline cellulose; polyethylene glycol, unspecified; povidone, unspecified; propylene glycol; sodium alginate; sodium citrate, unspecified form; talc; titanium dioxide

KIRKLAND SIGNATURE™ ALLERCLEAR® D 24 HR
Extended Release

Drug Facts

ACTIVE INGREDIENT

Active ingredients (in each tablet) | Purpose
Loratadine, USP 10 mg | Antihistamine
Pseudoephedrine sulfate, USP 240 mg | Nasal decongestant

Uses

- temporarily relieves these symptoms due to hay fever or other upper respiratory allergies:
  - sneezing
  - itchy, watery eyes
  - runny nose
  - itching of the nose or throat
- reduces swelling of nasal passages
- temporarily relieves sinus congestion and pressure
- temporarily relieves nasal congestion due to the common cold, hay fever or other upper respiratory allergies
- temporarily restores freer breathing through the nose

Warnings

Do not use

- if you have ever had an allergic reaction to this product or any of its ingredients
- If you are now taking a prescription monoamine oxidase inhibitor (MAOI) (certain drugs for depression, psychiatric, or emotional conditions, or Parkinson's disease), or for 2 weeks after stopping the MAOI drug. If you do not know if your prescription drug contains an MAOI, ask a doctor or pharmacist before taking this product.

Ask a doctor before use if you have

- heart disease
- thyroid disease
- high blood pressure
- diabetes
- trouble urinating due to an enlarged prostate gland
- liver or kidney disease. Your doctor should determine if you need a different dose.

When using this product do not take more than directed. Taking more than directed may cause drowsiness.

Stop use and ask a doctor if

- an allergic reaction to this product occurs. Seek medical help right away.
- symptoms do not improve within 7 days or are accompanied by a fever
- nervousness, dizziness or sleeplessness occurs

PREGNANCY OR BREAST FEEDING

If pregnant or breast-feeding, ask a health professional before use.

Keep out of reach of children. In case of overdose, get medical help or contact a Poison Control Center right away (1-800-222-1222).

Directions

- do not divide, crush, chew or dissolve the tablet

adults and children 12 years and over | 1 tablet daily with a full glass of water; not more than 1 tablet in 24 hours
children under 12 years of age | ask a doctor
consumers with liver or kidney disease | ask a doctor

Other information

- sodium: contains 10 mg/tablet
- calcium: contains 25 mg/tablet
- TAMPER EVIDENT: DO NOT USE IF BLISTER UNITS ARE TORN, BROKEN OR SHOW ANY SIGNS OF TAMPERING.
- store between 20° C to 25° C (68° F to 77° F)
- protect from light and store in a dry place

Inactive ingredients

calcium carbonate, colloidal silicon dioxide, hydroxypropyl cellulose, hypromellose, iron oxide black, lactose monohydrate, magnesium stearate, microcrystalline cellulose, polyethylene glycol, povidone, pregelatinized starch, propylene glycol, shellac glaze, sodium alginate, sodium citrate, talc and titanium dioxide

Questions?

call 1-800-406-7984

Manufactured by:
Ohm Laboratories Inc.
1385 Livingston Avenue
North Brunswick, NJ 08902
For Costco Wholesale Corporation
P.O. Box 34535
Seattle, WA 98124-1535 USA
1-800-774-2678
www.costco.com

**All trademarks are property of their respective owners. This product is not affiliated with the makers/owners of Claritin-D.®

PRINCIPAL DISPLAY PANEL - 15 Tablet Blister Pack Carton

KIRKLAND
Signature™

COMPARE TO
CLARITIN-D® 24 HOUR
active ingredients**

NDC 63981-724-15
ITM. / ART. 1133953

ALLERGY & CONGESTION
NON-DROWSY*

ALLERCLEAR® D-24 hr

Pseudoephedrine Sulfate, USP 240 mg/Nasal Decongestant
Loratadine, USP 10 mg/Antihistamine
Extended-Release Tablets

Indoor & Outdoor Allergies

Actual Size

24 Hour Relief of:

• Nasal & Sinus Congestion due to Colds or Allergies
• Sneezing • Runny Nose
• Itchy, Watery Eyes
• Itchy Throat or Nose due to Allergies

*When taken as directed. See drug facts panel.

15
EXTENDED
RELEASE TABLETS